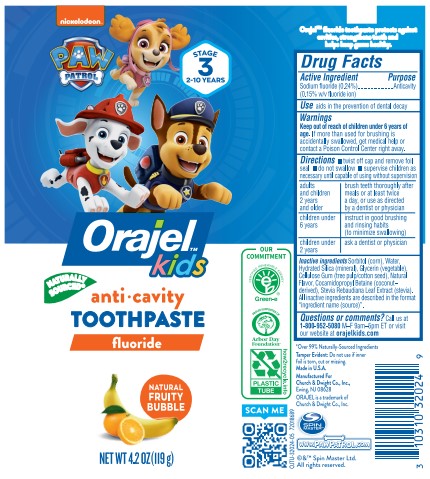 DRUG LABEL: Orajel Paw Patrol
NDC: 10237-786 | Form: PASTE, DENTIFRICE
Manufacturer: Church & Dwight Co., Inc.
Category: otc | Type: HUMAN OTC DRUG LABEL
Date: 20241127

ACTIVE INGREDIENTS: SODIUM FLUORIDE 1.5 mg/1 g
INACTIVE INGREDIENTS: HYDRATED SILICA; METHYL SALICYLATE; CARBOXYMETHYLCELLULOSE SODIUM, UNSPECIFIED; SACCHARIN SODIUM; SODIUM LAURYL SULFATE; FD&C BLUE NO. 1; SORBITOL; WATER; POLYETHYLENE GLYCOL 400

Orajel Paw Patrol Anticavity Fluoride Toothpaste

ACTIVE INGREDIENT

Sodium fluoride 0.24%

(0.15% w/v fluoride ion)

PURPOSE

Anticavity toothpaste

INDICATIONS AND USAGE

aids in the prevention of dental decay

Keep out of reach of children under 6 years of age. If more than used for brushing is accidentally swallowed, get medical help or contact a Poison Control Center right away.

Keep out of reach of children under 6 years of age. If more than used for brushing is accidentally swallowed, get medical help or contact a Poison Control Center right away.

Directions

- twist off cap and remove foil seal
- do not swallow
- supervise children as necessary until capable of using without supervision

adults and children 2 years and older | brush teeth thoroughly after meals or at least twice a day, or use as directed by a dentist or physician
children under 6 years | instruct in good brushing and rinsing habits (to minimize swallowing)
children under 2 years | ask a dentist or physician

INACTIVE INGREDIENT

Sorbitol (corn), Water, Hydrated Silica (mineral), Glycerin (vegetable), Cellulose Gum (tree pulp/cotton seed), Natural Flavor, Cocamidopropyl Betaine (coconut-derived), Stevia Rebaudiana Leaf Extract (stevia). All inactive ingredients are described in the format "ingredient name (source)".

Questions or comments?

Call us at 1-800-952-5080 M-F 9am - 5pm ET or visit our website at www.orajelkids.com

PACKAGE LABEL

nickelodeon™

PAW

PATROL

STAGE

3

2-10 YEARS

Orajel™

kids

NATURALLY

SOURCED*

anti · cavity

TOOTHPASTE

fluoride

NATURAL

FRUITY

BUBBLE

NET WT 4.2 OZ (119 g)